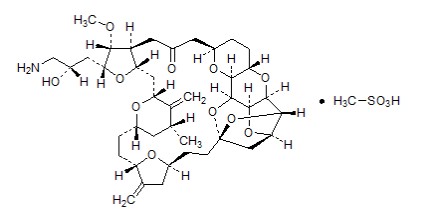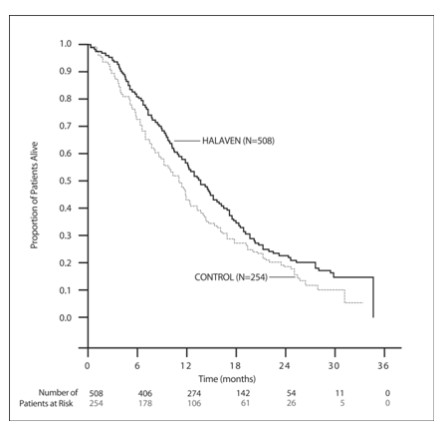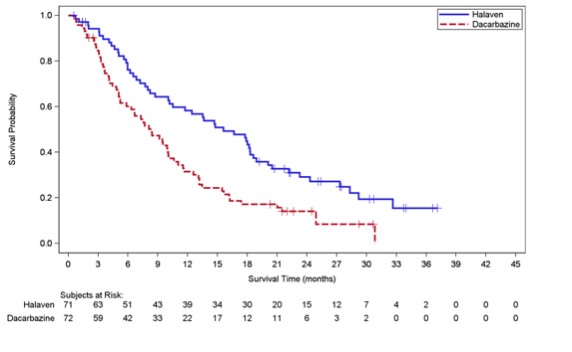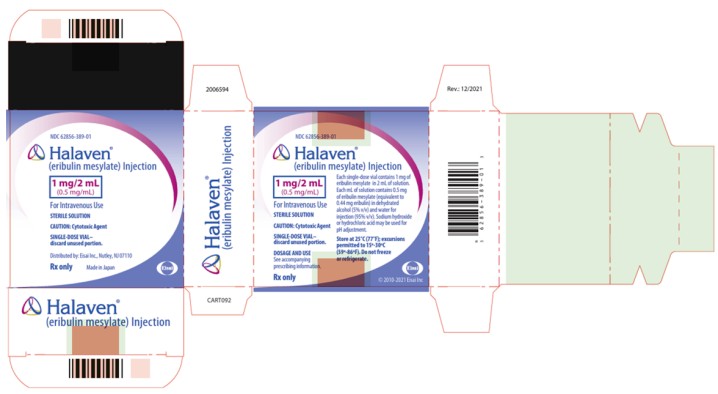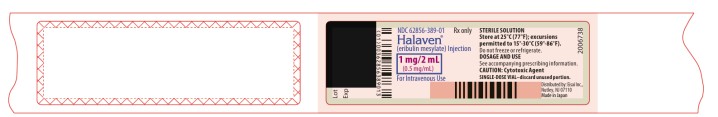 DRUG LABEL: Halaven
NDC: 62856-389 | Form: INJECTION
Manufacturer: Eisai Inc.
Category: prescription | Type: HUMAN PRESCRIPTION DRUG LABEL
Date: 20251107

ACTIVE INGREDIENTS: ERIBULIN MESYLATE 0.5 mg/1 mL
INACTIVE INGREDIENTS: ALCOHOL; WATER; SODIUM HYDROXIDE; HYDROCHLORIC ACID

HIGHLIGHTS OF PRESCRIBING INFORMATION

These highlights do not include all the information needed to use HALAVEN safely and effectively. See full prescribing information for HALAVEN.
HALAVEN® (eribulin mesylate) injection, for intravenous use
Initial U.S. Approval: 2010

RECENT MAJOR CHANGES

Instructions for Preparation and Administration (2.3) 09/2021

1 INDICATIONS AND USAGE

HALAVEN is a microtubule inhibitor indicated for the treatment of patients with:

- Metastatic breast cancer who have previously received at least two chemotherapeutic regimens for the treatment of metastatic disease. Prior therapy should have included an anthracycline and a taxane in either the adjuvant or metastatic setting. (1.1)
- Unresectable or metastatic liposarcoma who have received a prior anthracycline-containing regimen. (1.2)

2 DOSAGE AND ADMINISTRATION

- Administer 1.4 mg/m2 intravenously over 2 to 5 minutes on Days 1 and 8 of a 21-day cycle. (2.1)
- Reduce dose in patients with hepatic impairment or with moderate or severe renal impairment. (2.1)
- Do not mix with other drugs or administer with dextrose-containing solutions. (2.3)

3 DOSAGE FORMS AND STRENGTHS

Injection: 1 mg per 2 mL (0.5 mg per mL) eribulin mesylate in a single-dose vial (3)

4 CONTRAINDICATIONS

None (4)

5 WARNINGS AND PRECAUTIONS

- Neutropenia: Monitor peripheral blood cell counts and adjust dose as appropriate. (5.1)
- Peripheral Neuropathy: Monitor for signs of neuropathy. Manage with dose delay and adjustment. (5.2)
- Embryo-Fetal Toxicity: Can cause fetal harm. Advise females of reproductive potential of the potential risk to the fetus and to use effective contraception. (5.3, 8.1, 8.3)
- QT Prolongation: Monitor for prolonged QT intervals in patients with congestive heart failure, bradyarrhythmias, drugs known to prolong the QT interval, and electrolyte abnormalities. Avoid in patients with congenital long QT syndrome. (5.4)

6 ADVERSE REACTIONS

The most common adverse reactions (≥25%) in metastatic breast cancer were neutropenia, anemia, asthenia/fatigue, alopecia, peripheral neuropathy, nausea, and constipation. (6.1)

The most common adverse reactions (≥25%) in liposarcoma and leiomyosarcoma were fatigue, nausea, alopecia, constipation, peripheral neuropathy, abdominal pain, and pyrexia. The most common (≥5%) Grade 3-4 laboratory abnormalities in liposarcoma and leiomyosarcoma were neutropenia, hypokalemia, and hypocalcemia. (6.1)

To report SUSPECTED ADVERSE REACTIONS, contact Eisai Inc. at (1-877-873-4724) or FDA at 1-800-FDA-1088 or www.fda.gov/medwatch.

8 USE IN SPECIFIC POPULATIONS

- Lactation: Do not breastfeed. (8.2)
- Hepatic Impairment: A lower starting dose is recommended for patients with mild (Child-Pugh A) and moderate (Child-Pugh B) hepatic impairment. Patients with severe hepatic impairment (Child-Pugh C) were not studied. (8.6)
- Renal Impairment: A lower starting dose is recommended for patients with moderate (CLcr 30-49 mL/min) or severe (CLcr 15-29 mL/min) renal impairment. (8.7)

FULL PRESCRIBING INFORMATION

1 INDICATIONS AND USAGE

1.1 Metastatic Breast Cancer

HALAVEN is indicated for the treatment of patients with metastatic breast cancer who have previously received at least two chemotherapeutic regimens for the treatment of metastatic disease. Prior therapy should have included an anthracycline and a taxane in either the adjuvant or metastatic setting [see Clinical Studies (14.1)].

1.2 Liposarcoma

HALAVEN is indicated for the treatment of patients with unresectable or metastatic liposarcoma who have received a prior anthracycline-containing regimen [see Clinical Studies (14.2)].

2 DOSAGE AND ADMINISTRATION

2.1 Recommended Dose

The recommended dose of HALAVEN is 1.4 mg/m^2 administered intravenously over 2 to 5 minutes on Days 1 and 8 of a 21-day cycle.

The recommended dose of HALAVEN in patients with mild hepatic impairment (Child-Pugh A) is 1.1 mg/m^2 administered intravenously over 2 to 5 minutes on Days 1 and 8 of a 21-day cycle [see Use in Specific Populations (8.6)].

The recommended dose of HALAVEN in patients with moderate hepatic impairment (Child-Pugh B) is 0.7 mg/m^2 administered intravenously over 2 to 5 minutes on Days 1 and 8 of a 21-day cycle [see Use in Specific Populations (8.6)].

The recommended dose of HALAVEN in patients with moderate or severe renal impairment (creatinine clearance (CLcr) 15-49 mL/min) is 1.1 mg/m^2 administered intravenously over 2 to 5 minutes on Days 1 and 8 of a 21-day cycle [see Use in Specific Populations (8.7)].

2.2 Dose Modification

Assess for peripheral neuropathy and obtain complete blood cell counts prior to each dose.

Recommended dose delays

- Do not administer HALAVEN on Day 1 or Day 8 for any of the following:
  - ANC < 1,000/mm^3
  - Platelets < 75,000/mm^3
  - Grade 3 or 4 non-hematological toxicities.
- The Day 8 dose may be delayed for a maximum of 1 week.
  - If toxicities do not resolve or improve to ≤ Grade 2 severity by Day 15, omit the dose.
  - If toxicities resolve or improve to ≤ Grade 2 severity by Day 15, administer HALAVEN at a reduced dose and initiate the next cycle no sooner than 2 weeks later.

Recommended dose reductions

- If a dose has been delayed for toxicity and toxicities have recovered to Grade 2 severity or less, resume HALAVEN at a reduced dose as set out in Table 1.
- Do not re-escalate HALAVEN dose after it has been reduced.

Table 1: Recommended Dose Reductions
Event Description | Recommended HALAVEN Dose
Permanently reduce the 1.4 mg/m^2 HALAVEN dose for any of the following: | 1.1 mg/m^2
ANC <500/mm^3 for >7 days
ANC <1,000 /mm^3 with fever or infection
Platelets <25,000/mm^3
Platelets <50,000/mm^3 requiring transfusion
Non-hematologic Grade 3 or 4 toxicities
Omission or delay of Day 8 HALAVEN dose in previous cycle for toxicity
Occurrence of any event requiring permanent dose reduction while receiving 1.1 mg/m^2 | 0.7 mg/m^2
Occurrence of any event requiring permanent dose reduction while receiving 0.7 mg/m^2 | Discontinue HALAVEN
ANC = absolute neutrophil count.
Toxicities graded in accordance with National Cancer Institute (NCI) Common Terminology Criteria for Adverse Events
(CTCAE) version 3.0.

2.3 Instructions for Preparation and Administration

Aseptically withdraw the required amount of HALAVEN from the single-dose vial and administer undiluted or diluted in 100 mL of 0.9% Sodium Chloride Injection, USP.

Do not dilute in or administer through an intravenous line containing solutions with dextrose. Do not administer in the same intravenous line concurrent with the other medicinal products.

Store undiluted HALAVEN in the syringe for up to 4 hours at room temperature or for up to 24 hours under refrigeration at 4°C (40°F). Store diluted solutions of HALAVEN for up to 4 hours at room temperature or up to 24 hours under refrigeration at 4°C (40°F).

Discard unused portions of the vial.

3 DOSAGE FORMS AND STRENGTHS

Injection: 1 mg/2 mL (0.5 mg/mL) eribulin mesylate is a clear, colorless, sterile solution in a single-dose vial.

4 CONTRAINDICATIONS

None.

5 WARNINGS AND PRECAUTIONS

5.1 Neutropenia

In Study 1, severe neutropenia (ANC < 500/mm3) lasting more than one week occurred in 12% (62/503) of patients with metastatic breast cancer, leading to discontinuation in <1% of patients. Febrile neutropenia (fever ≥38.5°C with Grade 3 or 4 neutropenia) occurred in 5% (23/503) of patients; two patients (0.4%) died from complications of febrile neutropenia [see Adverse Reactions (6.1)].

In Study 1, patients with alanine aminotransferase (ALT) or aspartate aminotransferase (AST) > 3 × ULN (upper limit of normal) experienced a higher incidence of Grade 4 neutropenia and febrile neutropenia than patients with normal aminotransferase levels. Patients with bilirubin > 1.5 × ULN also had a higher incidence of Grade 4 neutropenia and febrile neutropenia.

In Study 2, severe neutropenia (ANC < 500/mm3) lasting more than one week occurred in 12% (26/222) of patients with liposarcoma or leiomyosarcoma. Febrile neutropenia occurred in 0.9% of patients treated with HALAVEN and fatal neutropenic sepsis in 0.9% [see Adverse Reactions (6.1)].

Monitor complete blood counts prior to each dose; increase the frequency of monitoring in patients who develop Grade 3 or 4 cytopenias. Delay administration of HALAVEN and reduce subsequent doses in patients who experience febrile neutropenia or Grade 4 neutropenia lasting longer than 7 days [see Dosage and Administration (2.2)]. Clinical studies of HALAVEN did not include patients with baseline neutrophil counts below 1,500/mm^3.

5.2 Peripheral Neuropathy

In Study 1, Grade 3 peripheral neuropathy occurred in 8% (40/503) of patients, and Grade 4 in 0.4% (2/503) of patients with metastatic breast cancer (MBC). Peripheral neuropathy was the most common toxicity leading to discontinuation of HALAVEN (5% of patients; 24/503) in Study 1. Neuropathy lasting more than one year occurred in 5% (26/503) of patients. Twenty-two percent (109/503) of patients developed a new or worsening neuropathy that had not recovered within a median follow-up duration of 269 days (range 25-662 days).

In Study 2, Grade 3 peripheral neuropathy occurred in 3.1% (7/223) of HALAVEN-treated patients. Peripheral neuropathy led to discontinuation of HALAVEN in 0.9% of patients. The median time to first occurrence of peripheral neuropathy of any severity was 5 months (range: 3.5 months to 9 months). Neuropathy lasting more than 60 days occurred in 58% (38/65) of patients. Sixty three percent (41/65) had not recovered within a median follow-up duration of 6.4 months (range: 27 days to 29 months).

Monitor patients closely for signs of peripheral motor and sensory neuropathy. Withhold HALAVEN in patients who experience Grade 3 or 4 peripheral neuropathy, until resolution to Grade 2 or less [see Dosage and Administration (2.2)].

5.3 Embryo-Fetal Toxicity

Based on findings from an animal reproduction study and its mechanism of action, HALAVEN can cause fetal harm when administered to a pregnant woman. There are no adequate and well-controlled studies of HALAVEN in pregnant women. In animal reproduction studies, eribulin mesylate caused embryo-fetal toxicity when administered to pregnant rats during organogenesis at doses below the recommended human dose. Advise pregnant women of the potential risk to a fetus. Advise females of reproductive potential to use effective contraception during treatment with HALAVEN and for at least 2 weeks following the final dose. Advise males with female partners of reproductive potential to use effective contraception during treatment with HALAVEN and for 3.5 months following the final dose [see Use in Specific Populations (8.1)].

5.4 QT Prolongation

In an uncontrolled open-label ECG study in 26 patients, QT prolongation was observed on Day 8, independent of eribulin concentration, with no QT prolongation observed on Day 1. ECG monitoring is recommended if therapy is initiated in patients with congestive heart failure, bradyarrhythmias, drugs known to prolong the QT interval, including Class Ia and III antiarrhythmics, and electrolyte abnormalities. Correct hypokalemia or hypomagnesemia prior to initiating HALAVEN and monitor these electrolytes periodically during therapy. Avoid HALAVEN in patients with congenital long QT syndrome.

6 ADVERSE REACTIONS

6.1 Clinical Trials Experience

Because clinical trials are conducted under widely varying conditions, the adverse reaction rates observed in the clinical trials of a drug cannot be directly compared to rates in other clinical trials and may not reflect the rates observed in clinical practice.

The following adverse reactions are discussed in detail in other sections of the labeling:

- Neutropenia [see Warnings and Precautions (5.1)]
- Peripheral neuropathy [see Warnings and Precautions (5.2)]
- QT prolongation [see Warnings and Precautions (5.4)]

In clinical trials, HALAVEN has been administered to 1963 patients including 467 patients exposed to HALAVEN for 6 months or longer. The majority of the 1963 patients were women (92%) with a median age of 55 years (range: 17 to 85 years). The racial and ethnic distribution was White (72%), Black (4%), Asian (9%), and other (3%).

Metastatic Breast Cancer

The most common adverse reactions (≥25%) reported in patients receiving HALAVEN were neutropenia, anemia, asthenia/fatigue, alopecia, peripheral neuropathy, nausea, and constipation. The most common serious adverse reactions reported in patients receiving HALAVEN were febrile neutropenia (4%) and neutropenia (2%). The most common adverse reaction resulting in discontinuation of HALAVEN was peripheral neuropathy (5%).

The adverse reactions described in Table 2 were identified in 750 patients treated in Study 1 [see Clinical Studies (14.1)]. In Study 1, patients were randomized (2:1) to receive either HALAVEN (1.4 mg/m^2 on Days 1 and 8 of a 21-day cycle) or single agent treatment chosen by their physician (control group). A total of 503 patients received HALAVEN and 247 patients in the control group received therapy consisting of chemotherapy [total 97% (anthracyclines 10%, capecitabine 18%, gemcitabine 19%, taxanes 15%, vinorelbine 25%, other chemotherapies 10%)] or hormonal therapy (3%). The median duration of exposure was 118 days for patients receiving HALAVEN and 63 days for patients receiving control therapy. Table 2 reports the most common adverse reactions occurring in at least 10% of patients in either group.

Table 2: Adverse Reactionsa with a Per-Patient Incidence of at Least 10% in Study 1
Adverse Reactions | HALAVEN n=503 |  | Control Group n=247
 | All Grades | ≥ Grade 3 | All Grades | ≥ Grade 3
Blood and lymphatic system disordersb
Neutropenia | 82% | 57% | 53% | 23%
Anemia | 58% | 2% | 55% | 4%
Nervous system disorders
Peripheral neuropathyc | 35% | 8% | 16% | 2%
Headache | 19% | <1% | 12% | <1%
General disorders
Asthenia/Fatigue | 54% | 10% | 40% | 11%
Pyrexia | 21% | <1% | 13% | <1%
Mucosal inflammation | 9% | 1% | 10% | 2%
Gastrointestinal disorders
Nausea | 35% | 1% | 28% | 3%
Constipation | 25% | 1% | 21% | 1%
Vomiting | 18% | 1% | 18% | 1%
Diarrhea | 18% | 0 | 18% | 0
Musculoskeletal and connective tissue disorders
Arthralgia/Myalgia | 22% | <1% | 12% | 1%
Back pain | 16% | 1% | 7% | 2%
Bone pain | 12% | 2% | 9% | 2%
Pain in extremity | 11% | 1% | 10% | 1%
Metabolism and nutrition disorders
Decreased weight | 21% | 1% | 14% | <1%
Anorexia | 20% | 1% | 13% | 1%
Respiratory, thoracic, and mediastinal disorders
Dyspnea | 16% | 4% | 13% | 4%
Cough | 14% | 0 | 9% | 0
Skin and subcutaneous tissue disorders
Alopecia | 45% | NAd | 10% | NAd
Infections
Urinary Tract Infection | 10% | 1% | 5% | 0
a adverse reactions were graded per National Cancer Institute Criteria for Adverse Events version 4.0.
b based upon laboratory data.
c includes peripheral neuropathy, peripheral sensorimotor neuropathy, peripheral motor neuropathy, polyneuropathy, peripheral sensory neuropathy, and paraesthesia.
d not applicable; (grading system does not specify > Grade 2 for alopecia).

Cytopenias: Grade 3 neutropenia occurred in 28% (143/503) of patients who received HALAVEN in Study 1, and 29% (144/503) of patients experienced Grade 4 neutropenia. Febrile neutropenia occurred in 5% (23/503) of patients; two patients (0.4%) died from complications of febrile neutropenia. Dose reduction due to neutropenia was required in 12% (62/503) of patients and discontinuation was required in <1% of patients. The mean time to nadir was 13 days and the mean time to recovery from severe neutropenia (<500/mm^3) was 8 days. Grade 3 or greater thrombocytopenia occurred in 1% (7/503) of patients. G-CSF (granulocyte colony-stimulating factor) or GM-CSF (granulocyte–macrophage colony-stimulating factor) was used in 19% of patients who received HALAVEN.

Peripheral Neuropathy: In Study 1, 17% of enrolled patients had Grade 1 peripheral neuropathy and 3% of patients had Grade 2 peripheral neuropathy at baseline. Dose reduction due to peripheral neuropathy was required by 3% (14/503) of patients who received HALAVEN. Four percent (20/503) of patients experienced peripheral motor neuropathy of any grade and 2% (8/503) of patients developed Grade 3 peripheral motor neuropathy.

Liver Function Test Abnormalities: Among patients with Grade 0 or 1 ALT levels at baseline, 18% of HALAVEN-treated patients experienced Grade 2 or greater ALT elevation. One HALAVEN-treated patient without documented liver metastases had concomitant Grade 2 elevations in bilirubin and ALT; these abnormalities resolved and did not recur with re-exposure to HALAVEN.

Less Common Adverse Reactions: The following additional adverse reactions were reported in ≥5% to <10% of the HALAVEN-treated group:

- Eye Disorders: increased lacrimation
- Gastrointestinal Disorders: dyspepsia, abdominal pain, stomatitis, dry mouth
- General Disorders and Administration Site Conditions: peripheral edema
- Infections and Infestations: upper respiratory tract infection
- Metabolism and Nutrition Disorders: hypokalemia
- Musculoskeletal and Connective Tissue Disorders: muscle spasms, muscular weakness
- Nervous System Disorders: dysgeusia, dizziness
- Psychiatric Disorders: insomnia, depression
- Skin and Subcutaneous Tissue Disorders: rash

Liposarcoma

The safety of HALAVEN was evaluated in Study 2, an open-label, randomized, multicenter, active-controlled trial, in which patients were randomized (1:1) to receive either HALAVEN 1.4 mg/m^2 on Days 1 and 8 of a 21-day cycle or dacarbazine at doses of 850 mg/m^2 (20%), 1000 mg/m^2 (64%), or 1200 mg/m^2 (16%) every 3 weeks. A total of 223 patients received HALAVEN and 221 patients received dacarbazine. Patients were required to have received at least two prior systemic chemotherapy regimens. The trial excluded patients with pre-existing ≥ Grade 3 peripheral neuropathy, known central nervous system metastasis, elevated serum bilirubin or significant chronic liver disease, history of myocardial infarction within 6 months, history of New York Heart Association Class II or IV heart failure, or cardiac arrhythmia requiring treatment. The median age of the safety population in Study 2 was 56 years (range: 24 to 83 years); 67% female; 73% White, 3% Black or African American, 8% Asian/Pacific Islander, and 15% unknown; 99% received prior anthracycline-containing regimen; and 99% received ≥ 2 prior regimens. The median duration of exposure was 2.3 months (range: 21 days to 26 months) for patients receiving HALAVEN [see Clinical Studies (14.2)].

The most common adverse reactions (≥25%) reported in patients receiving HALAVEN were fatigue, nausea, alopecia, constipation, peripheral neuropathy, abdominal pain, and pyrexia. The most common (≥5%) Grade 3-4 laboratory abnormalities reported in patients receiving HALAVEN were neutropenia, hypokalemia, and hypocalcemia. The most common serious adverse reactions reported in patients receiving HALAVEN were neutropenia (4.9%) and pyrexia (4.5%). Permanent discontinuation of HALAVEN for adverse reactions occurred in 8% of patients. The most common adverse reactions resulting in discontinuation of HALAVEN were fatigue and thrombocytopenia (0.9% each). Twenty-six percent of patients required at least one dose reduction. The most frequent adverse reactions that led to dose reduction were neutropenia (18%) and peripheral neuropathy (4.0%).

Table 3 summarizes the incidence of adverse reactions occurring in at least 10% of patients in the HALAVEN-treated arm in Study 2.

Table 3: Adverse Reactionsa Occurring in ≥10% (all Grades) of Patients Treated on the HALAVEN arm and at a Higher Incidence than in the Dacarbazine Arm (Between Arm Difference of ≥5% for All Grades or ≥2% for Grades 3 and 4) (Study 2)b
Adverse Reaction | HALAVEN n=223 |  | Dacarbazine n=221
 | All Grades | Grades 3-4 | All Grades | Grades 3-4
Nervous system disorders
Peripheral Neuropathyc | 29% | 3.1% | 8% | 0.5%
Headache | 18% | 0% | 10% | 0%
General disorders
Pyrexia | 28% | 0.9% | 14% | 0.5%
Gastrointestinal disorders
Constipation | 32% | 0.9% | 26% | 0.5%
Abdominal paind | 29% | 1.8% | 23% | 4.1%
Stomatitis | 14% | 0.9% | 5% | 0.5%
Skin and subcutaneous tissue disorders
Alopecia | 35% | NAe | 2.7% | NAe
Infections
Urinary tract infection | 11% | 2.2% | 5% | 0.5%
a Adverse reactions were graded per National Cancer Institute Criteria for Adverse Events version 4.03 (NCI CTCAE v4.03).
b Safety data from one study site enrolling six patients were excluded.
c Includes peripheral neuropathy, peripheral sensorimotor neuropathy, peripheral motor neuropathy, polyneuropathy, peripheral sensory neuropathy, and paraesthesia.
d Includes abdominal pain, upper abdominal pain, lower abdominal pain, abdominal discomfort.
e Not applicable; (grading system does not specify > Grade 2 for alopecia).

Other clinically important adverse reactions occurring in ≥10% of the HALAVEN-treated patients were:

- Gastrointestinal Disorders: nausea (41%); vomiting (19%), diarrhea (17%)
- General Disorders: asthenia/fatigue (62%); peripheral edema (12%)
- Metabolism and Nutrition Disorders: decreased appetite (19%)
- Musculoskeletal and Connective Tissue Disorders: arthralgia/myalgia (16%); back pain (16%)
- Respiratory Disorders: cough (18%)

Less Common Adverse Reactions: The following additional clinically important adverse reactions were reported in ≥5% to <10% of the HALAVEN-treated group:

- Blood and Lymphatic System Disorders: thrombocytopenia
- Eye Disorders: increased lacrimation
- Gastrointestinal Disorders: dyspepsia
- Metabolism and Nutrition Disorders: hyperglycemia
- Musculoskeletal and Connective Tissue Disorders: muscle spasms, musculoskeletal pain
- Nervous System Disorders: dizziness, dysgeusia
- Psychiatric Disorders: insomnia, anxiety
- Respiratory, Thoracic, and Mediastinal Disorders: oropharyngeal pain
- Vascular Disorders: hypotension

Table 4: Laboratory Abnormalities Occurring in ≥10% (all Grades) of Patients Treated on the HALAVEN arm and at a Higher Incidence than in the Dacarbazine Arm (Between Arm Difference of ≥5% for All Grades or ≥2% for Grades 3 and 4)a (Study 2)†
Laboratory Abnormality | Halaven |  | Dacarbazine
 | All Grades | Grades 3 - 4 | All Grades | Grades 3 – 4
Hematology
Anemia | 70% | 4.1% | 52% | 6%
Neutropenia | 63% | 32% | 30% | 8.9%
Chemistry
Increased alanine aminotransferase (ALT) | 43% | 2.3% | 28% | 2.3%
Increased aspartate aminotransferase (AST) | 36% | 0.9% | 16% | 0.5%
Hypokalemia | 30% | 5.4% | 14% | 2.8%
Hypocalcemia | 28% | 5% | 18% | 1.4%
Hypophosphatemia | 20% | 3.2% | 11% | 1.4%
a Each test incidence is based on the number of patients who had both baseline and at least one on-study measurement and at least 1 grade increase from baseline. Halaven group (range 221-222) and dacarbazine group (range 214-215).
† Laboratory results were graded per NCI CTCAE v4.03.

6.2 Postmarketing Experience

The following adverse drug reactions have been identified during post-approval of HALAVEN. Because these reactions are reported voluntarily from a population of uncertain size, it is not always possible to reliably estimate their frequency or establish a causal relationship to drug exposure.

- Blood and Lymphatic System Disorders: lymphopenia
- Gastrointestinal Disorders: pancreatitis
- Hepatobiliary Disorders: hepatotoxicity
- Immune System Disorders: drug hypersensitivity
- Infections and Infestations: pneumonia, sepsis/neutropenic sepsis
- Metabolism and Nutrition Disorders: hypomagnesemia, dehydration
- Respiratory, thoracic and mediastinal disorders: interstitial lung disease
- Skin and Subcutaneous Tissue Disorders: pruritus, Stevens-Johnson syndrome, toxic epidermal necrolysis

7 DRUG INTERACTIONS

7.1 Effects of Other Drugs on HALAVEN

No drug-drug interactions are expected with CYP3A4 inhibitors, CYP3A4 inducers or P-glycoprotein (P-gp) inhibitors. Clinically meaningful differences in exposure (AUC) were not observed in patients with advanced solid tumors when HALAVEN was administered with or without ketoconazole (a strong inhibitor of CYP3A4 and a P-gp inhibitor) and when HALAVEN was administered with or without rifampin (a CYP3A4 inducer) [see Clinical Pharmacology (12.3)].

7.2 Effects of HALAVEN on Other Drugs

Eribulin does not inhibit CYP1A2, CYP2C9, CYP2C19, CYP2D6, CYP2E1 or CYP3A4 enzymes or induce CYP1A2, CYP2C9, CYP2C19 or CYP3A4 enzymes at relevant clinical concentrations. Eribulin is not expected to alter the plasma concentrations of drugs that are substrates of these enzymes [see Clinical Pharmacology (12.3)].

8 USE IN SPECIFIC POPULATIONS

8.1 Pregnancy

Risk Summary

Based on findings from an animal reproduction study and its mechanism of action, HALAVEN can cause fetal harm when administered to a pregnant woman [see Clinical Pharmacology (12.1)]. There are no available data on the use of HALAVEN during pregnancy. In an animal reproduction study, eribulin mesylate caused embryo-fetal toxicity when administered to pregnant rats during organogenesis at doses below the recommended human dose [see Data]. Advise pregnant women of the potential risk to a fetus.

The estimated background risks of major birth defects and miscarriage for the indicated populations are unknown. In the U.S. general population, the estimated background risk of major birth defects and miscarriage in clinically-recognized pregnancies is 2% to 4% and 15% to 20%, respectively.

Data

Animal Data

In an embryo-fetal developmental toxicity study, pregnant rats received intravenous infusion of eribulin mesylate during organogenesis (Gestation Days 8, 10, and 12) at doses approximately 0.04, 0.13, 0.43 and 0.64 times the recommended human dose, based on body surface area. Increased abortion and severe fetal external or soft tissue malformations, including the absence of a lower jaw and tongue, or stomach and spleen, were observed at doses 0.64 times the recommended human dose of 1.4 mg/m^2 based on body surface area. Increased embryo-fetal death/resorption, reduced fetal weights, and minor skeletal anomalies consistent with developmental delay were also reported at doses at or above a maternally toxic dose of approximately 0.43 times the recommended human dose.

8.2 Lactation

Risk Summary

There is no information regarding the presence of eribulin mesylate or its metabolites in human milk, the effects on the breastfed infant, or the effects on milk production. No lactation studies in animals were conducted. Because of the potential for serious adverse reactions in breastfed infants from eribulin mesylate, advise women not to breastfeed during treatment with HALAVEN and for 2 weeks after the final dose.

8.3 Females and Males of Reproductive Potential

Contraception

Females

Based on findings from an animal reproduction study and its mechanism of action, HALAVEN can cause fetal harm when administered to a pregnant woman [see Use in Specific Populations (8.1)]. Advise females of reproductive potential to use effective contraception during treatment with HALAVEN and for at least 2 weeks following the final dose.

Males

Based on its mechanism of action, advise males with female partners of reproductive potential to use effective contraception during treatment with HALAVEN and for 3.5 months following the final dose.

Infertility

Males

Based on animal data, HALAVEN may result in damage to male reproductive tissues leading to impaired fertility of unknown duration [see Nonclinical Toxicology (13.1)].

8.4 Pediatric Use

The safety and effectiveness of HALAVEN in pediatric patients have not been established.

The safety and effectiveness of HALAVEN alone or in combination with irinotecan in pediatric patients were assessed but not established in three open-label studies (NCT02171260, NCT03441360, and NCT03245450) in 77 pediatric patients aged 2 to <17 years with relapsed or refractory solid tumors and lymphomas, excluding central nervous system tumors. No new safety signals were observed in these studies. The pharmacokinetics (PK) of eribulin were within range of values of adult patients with metastatic liposarcoma or other tumors given the same dose per body surface area.

8.5 Geriatric Use

Study 1 did not include sufficient numbers of subjects with metastatic breast cancer aged 65 years and older to determine whether they respond differently from younger subjects. Of the 827 subjects who received the recommended dose and schedule of HALAVEN in clinical studies with advanced breast cancer, 15% (121/827) were 65 and older, and 2% (17/827) patients were 75 and older. No overall differences in safety were observed between these subjects and younger subjects.

Clinical studies of HALAVEN did not include a sufficient number of subjects in Study 2 aged 65 years and older to determine whether they respond differently from younger subjects.

8.6 Hepatic Impairment

Administration of HALAVEN at a dose of 1.1 mg/m^2 to patients with mild hepatic impairment and 0.7 mg/m^2 to patients with moderate hepatic impairment resulted in similar exposure to eribulin as a dose of 1.4 mg/m^2 to patients with normal hepatic function. Therefore, a lower starting dose of 1.1 mg/m^2 is recommended for patients with mild hepatic impairment (Child-Pugh A) and of 0.7 mg/m^2 is recommended for patients with moderate hepatic impairment (Child-Pugh B). HALAVEN was not studied in patients with severe hepatic impairment (Child-Pugh C) [see Dosage and Administration (2.1), Clinical Pharmacology (12.3)].

8.7 Renal Impairment

For patients with moderate or severe renal impairment (CLcr 15-49 mL/min), reduce the starting dose to 1.1 mg/m^2 [see Dosage and Administration (2.1), Clinical Pharmacology (12.3)].

10 OVERDOSAGE

Overdosage of HALAVEN has been reported at approximately 4 times the recommended dose, which resulted in Grade 3 neutropenia lasting seven days and a Grade 3 hypersensitivity reaction lasting one day.

There is no known antidote for HALAVEN overdose.

11 DESCRIPTION

HALAVEN contains eribulin mesylate, a microtubule dynamics inhibitor. Eribulin mesylate is a synthetic analogue of halichondrin B, a product isolated from the marine sponge Halichondria okadai. The chemical name for eribulin mesylate is 11,15:18,21:24,28-Triepoxy-7,9-ethano-12,15-methano-9H,15H-furo[3,2-i]furo[2',3':5,6]pyrano[4,3-b][1,4]dioxacyclopentacosin-5(4H)-one, 2-[(2S)-3-amino-2-hydroxypropyl]hexacosahydro-3-methoxy-26-methyl-20,27-bis(methylene)-, (2R,3R,3aS,7R,8aS,9S,10aR,11S,12R,13aR,13bS,15S,18S,21S,24S,26R,28R,29aS)-, methanesulfonate (salt). It has a molecular weight of 826.0 (729.9 for free base). The empirical formula is C40H59NO11•CH4O3S. Eribulin mesylate has the following structural formula:

HALAVEN is a clear, colorless, sterile solution for intravenous administration. Each single-dose vial contains 1 mg of eribulin mesylate in 2 mL of solution. Each mL of solution contains 0.5 mg of eribulin mesylate (equivalent to 0.44 mg eribulin) in dehydrated alcohol (5% v/v) and water for injection (95% v/v). Sodium hydroxide or hydrochloric acid may be used for pH adjustment.

12 CLINICAL PHARMACOLOGY

12.1 Mechanism of Action

Eribulin inhibits the growth phase of microtubules without affecting the shortening phase and sequesters tubulin into nonproductive aggregates. Eribulin exerts its effects via a tubulin-based antimitotic mechanism leading to G2/M cell-cycle block, disruption of mitotic spindles, and, ultimately, apoptotic cell death after prolonged mitotic blockage.

In addition, eribulin treatment of human breast cancer cells caused changes in morphology and gene expression as well as decreased migration and invasiveness in vitro. In mouse xenograft models of human breast cancer, eribulin treatment was associated with increased vascular perfusion and permeability in the tumor cores, resulting in reduced tumor hypoxia, and changes in the expression of genes in tumor specimens associated with a change in phenotype.

12.2 Pharmacodynamics

Cardiac Electrophysiology

The effect of HALAVEN on the QTc interval was assessed in an open-label, uncontrolled, multicenter, single-arm dedicated QT trial. A total of 26 patients with solid tumors received 1.4 mg/m^2 of HALAVEN on Days 1 and 8 of a 21-day cycle. A delayed QTc prolongation was observed on Day 8, with no prolongation observed on Day 1. The maximum mean QTcF change from baseline (95% upper confidence interval) was 11.4 (19.5) ms.

12.3 Pharmacokinetics

The pharmacokinetics (PK) of eribulin is linear with a mean elimination half-life of approximately 40 hours, a mean volume of distribution of 43 L/m^2 to 114 L/m^2 and mean clearance of 1.16 L/hr/m^2 to 2.42 L/hr/m^2 over the dose range of 0.25 mg/m^2 to 4.0 mg/m^2. The human plasma protein binding of eribulin at concentrations of 100 ng/mL to 1,000 ng/mL ranges from 49% to 65%. Eribulin exposure after multiple dosing is comparable to that following a single dose. No accumulation of eribulin is observed with weekly administration.

Elimination

Metabolism

Unchanged eribulin was the major circulating species in plasma following administration of ^14C-eribulin to patients. Metabolite concentrations represented <0.6% of parent compound, confirming that there are no major human metabolites of eribulin. Cytochrome P450 3A4 (CYP3A4) negligibly metabolizes eribulin in vitro.

Excretion

Eribulin is eliminated primarily in feces unchanged. After administration of ^14C-eribulin to patients, approximately 82% of the dose was eliminated in feces and 9% in urine. Unchanged eribulin accounted for approximately 88% and 91% of total eribulin in feces and urine, respectively.

Specific Populations

Age, Sex, and Race/Ethnicity: Based on a population pharmacokinetic analysis, no clinically meaningful differences in the pharmacokinetics of eribulin were observed based on age, sex, or race.

Hepatic Impairment

In a study evaluating the effect of hepatic impairment on the PK of eribulin, eribulin exposures increased by 1.8-fold in patients with mild hepatic impairment (Child-Pugh A; n=7) and by 2.5-fold in patients with moderate (Child-Pugh B; n=5) hepatic impairment as compared to patients with normal hepatic function (n=6). Administration of HALAVEN at a dose of 1.1 mg/m^2 to patients with mild hepatic impairment and 0.7 mg/m^2 to patients with moderate hepatic impairment resulted in similar exposure to eribulin at a dose of 1.4 mg/m^2 to patients with normal hepatic function [see Dosage and Administration (2.1), Use in Specific Populations (8.6)].

Renal Impairment

In a study evaluating the effect of renal impairment on the PK of eribulin, patients with moderate (CLcr 30-49 mL/min; n=7) and severe renal impairment (CLcr 15-29 mL/min; n=6) had 1.5-fold higher eribulin dose-normalized exposures compared to that in patients with normal renal function (CLcr ≥ 80 mL/min; n=6). There were no clinically meaningful changes in patients with mild renal impairment (CLcr 50-79 mL/min; n=27) [see Dosage and Administration (2.1), Use in Specific Populations (8.7)].

Drug Interaction Studies

Effect of Strong Inhibitors or Inducers of CYP3A4 on Eribulin: The effect of a strong CYP3A4 inhibitor and a P-gp inhibitor, ketoconazole, on the PK of eribulin was studied in a crossover trial of 12 patients with advanced solid tumors. No clinically relevant PK interaction was observed when HALAVEN was administered with or without ketoconazole (the geometric mean ratio of the AUC: 0.97; 90% CI: 0.83, 1.12).

The effect of a CYP3A4 inducer, rifampin, on the PK of eribulin was studied in a crossover trial of 14 patients with advanced solid tumors. No clinically relevant PK interaction was observed when HALAVEN was administered with or without rifampin (the geometric mean ratio of the AUC: 1.10; 90 CI%: 0.91, 1.34).

Effect of Eribulin on CYP Substrates: Eribulin shows no induction potential for CYP1A, CYP2B6, CYP2C9, CYP2C19, and CYP3A in primary human hepatocytes. Eribulin inhibits CYP3A4 activity in human liver microsomes, but it is unlikely that eribulin will substantially increase the plasma levels of CYP3A4 substrates. No significant inhibition of CYP1A2, CYP2C9, CYP2C19, CYP2D6, or CYP2E1 was detected with eribulin concentrations up to 5 μM in pooled human liver microsomes. In vitro drug interaction studies indicate that eribulin does not inhibit drugs that are substrates of these enzymes and it is unlikely that eribulin will affect plasma levels of drugs that are substrates of CYP enzymes.

Effect of Transporters on Eribulin: In vitro data suggest that eribulin at clinically relevant concentrations is a substrate of P-gp, but is not a substrate of breast cancer resistance protein (BCRP), multidrug resistance proteins (MRP2, MRP4), bile salt extrusion pump (BSEP), organic anion transporting polypeptides (OATP1B1, OATP1B3), organic anion transporters (OAT1, OAT3), organic cation transporters (OCT1, OCT2), or multidrug and toxin extrusion 1 (MATE1).

Effect of Eribulin on Transporters: In vitro data suggest that eribulin at clinically relevant concentrations may inhibit P-gp, but does not inhibit BCRP, OATP1B1, OCT1, OAT1, OAT3, or MATE1.

13 NONCLINICAL TOXICOLOGY

13.1 Carcinogenesis, Mutagenesis, Impairment of Fertility

Carcinogenicity studies have not been conducted with eribulin mesylate. Eribulin mesylate was not mutagenic in in vitro bacterial reverse mutation assays (Ames test). Eribulin mesylate was positive in mouse lymphoma mutagenesis assays, and was clastogenic in an in vivo rat bone marrow micronucleus assay.

Fertility studies have not been conducted with eribulin mesylate in humans or animals; however, nonclinical findings in repeat-dose dog and rat toxicology studies suggest that male fertility may be compromised by treatment with eribulin mesylate. Rats exhibited testicular toxicity (hypocellularity of seminiferous epithelium with hypospermia/aspermia) following dosing with eribulin mesylate at or above 0.43 times the recommended human dose (based on body surface area) given once weekly for 3 weeks, or at or above 0.21 times the recommended human dose (based on body surface area) given once weekly for 3 out of 5 weeks, repeated for 6 cycles. Testicular toxicity was also observed in dogs given 0.64 times the recommended human dose (based on body surface area) weekly for 3 out of 5 weeks, repeated for 6 cycles.

14 CLINICAL STUDIES

14.1 Metastatic Breast Cancer

Study 1 was an open-label, randomized, multicenter trial of 762 patients with metastatic breast cancer who received at least two chemotherapeutic regimens for the treatment of metastatic disease and experienced disease progression within 6 months of their last chemotherapeutic regimen. Patients were required to receive prior anthracycline- and taxane-based chemotherapy for adjuvant or metastatic disease. Patients were randomized (2:1) to receive HALAVEN (n=508) or a single agent therapy selected prior to randomization (control arm, n=254). Randomization was stratified by geographic region, HER2/neu status, and prior capecitabine exposure. HALAVEN was administered at a dose of 1.4 mg/m2 on Days 1 and 8 of a 21-day cycle. HALAVEN-treated patients received a median of 5 cycles (range: 1 to 23 cycles) of therapy. Control arm therapy consisted of 97% chemotherapy (26% vinorelbine, 18% gemcitabine, 18% capecitabine, 16% taxane, 9% anthracycline, 10% other chemotherapy), and 3% hormonal therapy. The main efficacy outcome was overall survival.

Patient demographic and baseline characteristics were comparable between the treatment arms. The median age was 55 (range: 27 to 85 years) and 92% were White. Sixty-four percent of patients were enrolled in North America/Western Europe/Australia, 25% in Eastern Europe/Russia, and 11% in Latin America/South Africa. Ninety-one percent of patients had a baseline ECOG performance status of 0 or 1. Tumor prognostic characteristics, including estrogen receptor status (positive: 67%, negative: 28%), progesterone receptor status (positive: 49%, negative: 39%), HER2/neu receptor status (positive: 16%, negative: 74%), triple negative status (ER-, PR-, HER2/neu-: 19%), presence of visceral disease (82%, including 60% liver and 38% lung) and bone disease (61%), and number of sites of metastases (greater than two: 50%), were also similar in the HALAVEN and control arms. Patients received a median of four prior chemotherapy regimens in both arms.

In Study 1, a statistically significant improvement in overall survival was observed in patients randomized to the HALAVEN arm compared to the control arm (see Table 5). An updated, unplanned survival analysis, conducted when 77% of events had been observed (see Figure 1), was consistent with the primary analysis. In patients randomized to HALAVEN, the objective response rate by the RECIST criteria was 11% (95% CI: 8.6%, 14.3%) and the median response duration was 4.2 months (95% CI: 3.8, 5.0 months).

Table 5: Comparison of Overall Survival in HALAVEN and Control Arm - Study 1
Overall Survival | HALAVEN (n=508) | Control Arm (n=254)
Primary survival analysis
Number of deaths | 274 | 148
Median, months (95% CI) | 13.1 (11.8, 14.3) | 10.6 (9.3, 12.5)
Hazard Ratio (95% CI)a | 0.81 (0.66, 0.99)
P valueb | 0.041
Updated survival analysis
Number of deaths | 386 | 203
Median, months (95% CI) | 13.2 (12.1, 14.4) | 10.6 (9.2, 12.0)
CI = confidence interval
a Based on Cox proportional hazards model stratified by geographic region, HER2 status, and prior capecitabine therapy.
b Based on a log-rank test stratified by geographic region, HER2 status, and prior capecitabine therapy.

Figure 1: Updated Overall Survival Analysis for Study 1

14.2 Liposarcoma

The efficacy and safety of HALAVEN were evaluated in Study 2, an open-label, randomized (1:1), multicenter, active-controlled trial. Eligible patients were required to have unresectable, locally advanced or metastatic liposarcoma or leiomyosarcoma, at least two prior systemic chemotherapies (one of which must have included an anthracycline), and disease progression within 6 months of the most recent chemotherapy regimen. Patients were randomized to HALAVEN 1.4 mg/m^2 administered intravenously on Days 1 and 8 of a 21-day cycle or to dacarbazine at a dose of 850 mg/m^2, 1000 mg/m^2, or 1200 mg/m^2 administered intravenously every 21 days (dacarbazine dose was selected by the investigator prior to randomization). Treatment continued until disease progression or unacceptable toxicity. Randomization was stratified by histology (liposarcoma or leiomyosarcoma), number of prior therapies (2 vs. > 2), and geographic region (U.S. and Canada vs. Western Europe, Australia, and Israel vs. Eastern Europe, Latin America, and Asia). The major efficacy outcome measure was overall survival (OS). Additional efficacy outcome measures were progression-free survival (PFS) and confirmed objective response rate (ORR) as assessed by the investigator according to Response Evaluation Criteria in Solid Tumors (RECIST v1.1). Patients in the dacarbazine arm were not offered HALAVEN at the time of disease progression.

A total of 446 patients were randomized, 225 to the HALAVEN arm and 221 to the dacarbazine arm. The median age was 56 years (range: 24 to 83); 33% were male; 73% were White; 44% had ECOG performance status (PS) 0 and 53% had ECOG PS 1; 68% had leiomyosarcoma and 32% had liposarcoma; 39% were enrolled in U.S. and Canada (Region 1) and 46% were enrolled in Western Europe, Australia, and Israel (Region 2); and 47% received more than two prior systemic chemotherapies. The most common (>40%) prior systemic chemotherapies were doxorubicin (90%), ifosfamide (62%), gemcitabine (59%), trabectedin (50%), and docetaxel (48%).

Of the 143 patients with liposarcoma, the median age was 55 years (range: 32 to 83); 62% were male, 72% were White; 41% had ECOG PS of 0 and 53% had ECOG PS of 1; 35% were enrolled in Region 1 and 51% were enrolled in Region 2; and 44% received more than two prior systemic chemotherapies. The distribution of subtypes of liposarcoma, based on local histologic assessment, were 45% dedifferentiated, 37% myxoid/round cell, and 18% pleomorphic.

Study 2 demonstrated a statistically significant improvement in OS in patients randomized to HALAVEN compared with dacarbazine (see Table 6). There was no significant difference in progression-free survival in the overall population. Treatment effects of HALAVEN were limited to patients with liposarcoma based on pre-planned, exploratory subgroup analyses of OS and PFS (see Tables 6 and 7 and Figure 2). There was no evidence of efficacy of HALAVEN in patients with advanced or metastatic leiomyosarcoma in Study 2 (see Table 7).

Table 6: Efficacy Results for the Liposarcoma Stratum and All Patients* in Study 2a
 | Liposarcoma Stratum |  |  | All Patients*
 | Halaven (n=71) |  | Dacarbazine (n=72) | Halaven (n=225) | Dacarbazine (n=221)
Overall survival
Deaths, n (%) | 52 (73) |  | 63 (88) | 173 (77) | 179 (81)
Median, months (95% CI) | 15.6 (10.2, 18.6) |  | 8.4 (5.2, 10.1) | 13.5 (11.1, 16.5) | 11.3 (9.5, 12.6)
Hazard ratio (HR) (95% CI) | 0.51 (0.35, 0.75) |  |  | 0.75 (0.61, 0.94)
Stratified log-rank p value | N/A† |  |  | 0.011
Progression-free survival
Events, n (%) | 57 (80) |  | 59 (82) | 194 (86) | 185 (84)
Disease progression | 53 |  | 52 | 180 | 170
Death | 4 |  | 7 | 14 | 15
Median, months (95% CI) | 2.9 (2.6, 4.8) |  | 1.7 (1.4, 2.6) | 2.6 (2.0, 2.8) | 2.6 (1.7, 2.7)
HR (95% CI) | 0.52 (0.35, 0.78) |  |  | 0.86 (0.69, 1.06)
Objective response rate
Objective response rate (%) (95% CI) | 1.4 (0, 7.6) | 0 (0, 4.2) |  | 4.0 (1.8, 7.5) | 5.0 (2.5, 8.7)

a Efficacy data from one study site enrolling six patients were excluded.
*All patients = liposarcoma and leiomyosarcoma.
† N/A = not applicable

Figure 2: Kaplan-Meier Curves of Overall Survival in the Liposarcoma Stratum in Study 2

Table 7: Efficacy Results for the Leiomyosarcoma Stratum in Study 2a
 | Leiomyosarcoma Stratum
 | Halaven (n=154) | Dacarbazine (n=149)
Overall survival
Deaths, n (%) | 121 (79) | 116 (78)
Median, months (95% CI) | 12.8 (10.3, 14.8) | 12.3 (11.0, 15.1)
HR (95% CI) | 0.90 (0.69, 1.18)
Progression-free survival
Events, n (%) | 137 (89) | 126 (85)
Disease progression | 127 | 118
Death | 10 | 8
Median, months (95% CI) | 2.2 (1.5, 2.7) | 2.6 (2.2, 2.9)
HR (95% CI) | 1.05 (0.81, 1.35)
Objective response rate (%) (95% CI) | 5.2 (2.3, 10) | 7.4 (3.7, 12.8)

a Efficacy data from one study site enrolling six patients were excluded.

15 REFERENCES

1. OSHA Hazardous Drugs. OSHA. http://www.osha.gov/SLTC/hazardousdrugs/index.html

16 HOW SUPPLIED/STORAGE AND HANDLING

NDC 62856-389-01

Injection: 1 mg/2 mL, in a single-dose vial. One vial per carton.

Store at 25°C (77°F); excursions permitted to 15° to 30° C (59° to 86° F). Do not freeze or refrigerate. Store the vials in their original cartons.

HALAVEN injection is a cytotoxic drug. Follow applicable special handling and disposal procedures.¹

17 PATIENT COUNSELING INFORMATION

Advise the patient to read the FDA-approved patient labeling (Patient Information).

Neutropenia

Advise patients to contact their health care provider for a fever of 100.5°F or greater or other signs or symptoms of infection such as chills, cough, or burning or pain on urination [see Warnings and Precautions (5.1)].

Peripheral Neuropathy

Advise patients to inform their healthcare providers of new or worsening numbness, tingling and pain in their extremities [see Warnings and Precautions (5.2)].

Embryo-Fetal Toxicity

- Advise females of reproductive potential of the potential risk to a fetus and to inform their healthcare provider of a known or suspected pregnancy [see Warnings and Precautions (5.3), Use in Specific Populations (8.1)].
- Advise females of reproductive potential to use effective contraception during treatment with HALAVEN and for at least 2 weeks after the final dose [see Use in Specific Populations (8.3)].
- Advise males with female partners of reproductive potential to use effective contraception during treatment with HALAVEN and for 3.5 months following the final dose [see Use in Specific Populations (8.3)].

Lactation

Advise women not to breastfeed during treatment with HALAVEN and for 2 weeks after the final dose [see Use in Specific Populations (8.2)].

Distributed by:
Eisai Inc.
Nutley, NJ 07110

© 2010-2022 Eisai Inc.

PATIENT INFORMATION
HALAVEN® (HAL-ih-ven)
(eribulin mesylate)
injection, for intravenous use

What is the most important information I should know about HALAVEN?
HALAVEN can cause serious side effects, including:

- Low white blood cell count (neutropenia). This can lead to serious infections that could lead to death. Your healthcare provider will check your blood cell counts before you receive each dose of HALAVEN and during treatment. Call your healthcare provider right away if you develop any of these symptoms of infection:
  ° fever (temperature above 100.5°F)
  ° chills
  ° cough
  ° burning or pain when you urinate
- Numbness, tingling, or pain in your hands or feet (peripheral neuropathy). Peripheral neuropathy is common with HALAVEN and sometimes can be severe. Tell your healthcare provider if you have new or worsening symptoms of peripheral neuropathy.
- Your healthcare provider may delay, decrease your dose, or stop treatment with HALAVEN if you have side effects.

See “What are possible side effects of HALAVEN?” for more information about side effects.

What is HALAVEN?
HALAVEN is a prescription medicine used to treat people with:

- Breast cancer
  ° that has spread to other parts of the body, and
  ° who have already received certain types of anticancer medicines after the cancer has spread
- Liposarcoma
  ° that cannot be treated with surgery or has spread to other parts of the body, and
  ° who have received treatment with a certain type of anticancer medicine

It is not known if HALAVEN is safe and effective in children under 18 years of age.

Before you receive HALAVEN, tell your healthcare provider about all of your medical conditions, including if you:

- have liver or kidney problems
- have heart problems, including a problem called congenital long QT syndrome
- have low potassium or low magnesium in your blood
- are pregnant or plan to become pregnant. HALAVEN can harm your unborn baby. Tell your healthcare provider right away if you become pregnant or think you are pregnant during treatment with HALAVEN.
  ° Females who are able to become pregnant should use an effective birth control during treatment with HALAVEN and for at least 2 weeks after the final dose of HALAVEN.
  ° Males should use an effective form of birth control when having sex with female partners who are able to become pregnant during treatment with HALAVEN and for 3 1/2 months (14 weeks) after the final dose of HALAVEN.
- are breastfeeding or plan to breastfeed. It is not known if HALAVEN passes into your breast milk. Do not breastfeed during treatment with HALAVEN and for 2 weeks after the final dose of HALAVEN.

Tell your healthcare provider about all the medicines you take, including prescription and over-the-counter medicines, vitamins, and herbal supplements.

How will I receive HALAVEN?

- HALAVEN is given by intravenous (IV) injection in your vein.
- HALAVEN is given in “cycles” of treatment, with each cycle lasting 21 days.
- HALAVEN is usually given on day 1 and day 8 of a treatment cycle.

What are the possible side effects of HALAVEN?
HALAVEN may cause serious side effects, including:

- See “What is the most important information I should know about HALAVEN?”
- HALAVEN can cause changes in your heartbeat (called QT prolongation). This can cause irregular heartbeats. Your healthcare provider may do heart monitoring (electrocardiogram or ECG) or blood tests during your treatment with HALAVEN to check for heart problems.

The most common side effects of HALAVEN in people with breast cancer include:

- low white blood cell count (neutropenia)
- low red blood cell count (anemia)
- weakness or tiredness
- hair loss (alopecia)
- nausea
- constipation

The most common side effects of HALAVEN in people with liposarcoma include:

- tiredness
- nausea
- hair loss (alopecia)
- constipation
- stomach pain
- fever

Your healthcare provider will do blood tests before and during treatment while you are taking HALAVEN. The most common changes to blood tests in people with liposarcoma include:

- low white blood cell count (neutropenia)
- decreased blood levels of potassium or calcium

Tell your healthcare provider about any side effect that bothers you or that does not go away.
These are not all the possible side effects of HALAVEN. Call your doctor for medical advice about side effects. You may report side effects to FDA at 1-800-FDA-1088.

General information about HALAVEN
Medicines are sometimes prescribed for purposes other than those listed in a Patient Information leaflet. You can ask your pharmacist or healthcare provider for information about HALAVEN that is written for health professionals.

What are the ingredients in HALAVEN?
Active Ingredient: eribulin mesylate
Inactive Ingredients: dehydrated alcohol, water for injection, and sodium hydroxide or hydrochloric acid may be used for pH adjustment.
HALAVEN® is a registered trademark used by Eisai Inc. under license from Eisai R&D Management Co., Ltd.
Distributed by: Eisai Inc. Nutley, NJ 07110
© 2010-2022 Eisai Inc.
For more information, go to www.HALAVEN.com or call Eisai Inc. at 1-877-873-4724. If you would like a leaflet with larger printing, please contact Eisai Inc. at 1-877-873-4724.

This Patient Information has been approved by the U.S. Food and Drug Administration. Revised: 09/2022

PACKAGE LABEL

PRINCIPAL DISPLAY PANEL

NDC 62856-389-01
Halaven®
(eribulin mesylate) Injection
1 mg/2 mL
(0.5 mg/mL)
For Intravenous Use